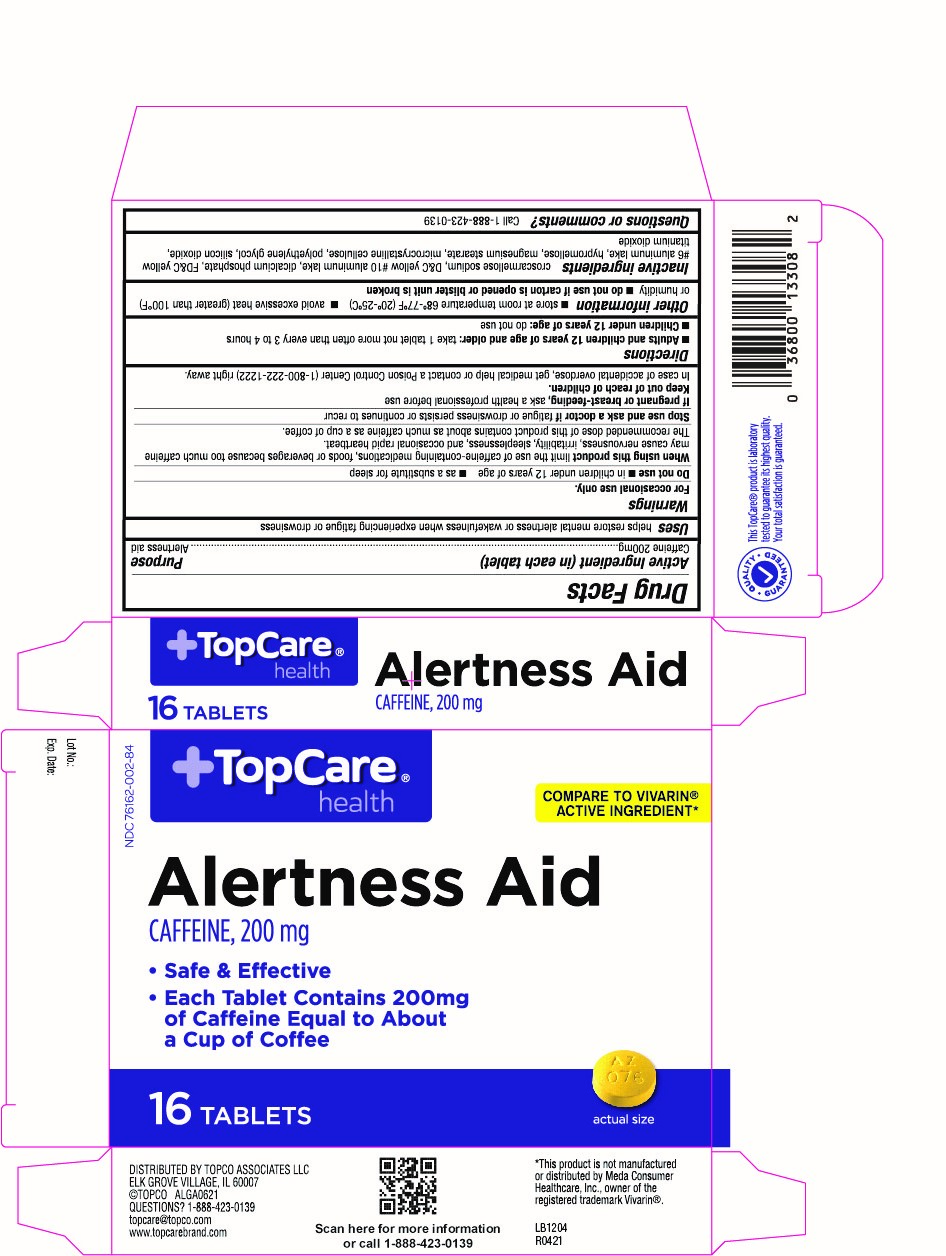 DRUG LABEL: Topcare Stay Awake
NDC: 76162-002 | Form: TABLET, COATED
Manufacturer: TopCo Associates, LLC
Category: otc | Type: HUMAN OTC DRUG LABEL
Date: 20210428

ACTIVE INGREDIENTS: CAFFEINE 200 mg/1 1
INACTIVE INGREDIENTS: CROSCARMELLOSE SODIUM; D&C YELLOW NO. 10; FD&C YELLOW NO. 6; HYPROMELLOSES; MAGNESIUM STEARATE; MICROCRYSTALLINE CELLULOSE; POLYETHYLENE GLYCOL, UNSPECIFIED; SILICON DIOXIDE; TITANIUM DIOXIDE

076 - Alertness Aid

Active ingredient(s)

Caffeine 200mg

Purpose

Alertness aid

Use

helps restore mental alertness or wakefulness when experiencing fatigue or drowsiness

Warnings

For occasional use only.

Do not use

- in children under 12 years of age
- as a substitute for sleep

When using this product

limit the use of caffeine-containing medications, foods or beverages because too much caffeine may cause nervousness, irritability, sleeplessness, and ocassionally rapid heartbeat.

The recommended dose of this product contains about as much caffeine as a cup of coffee.

Stop use and ask a doctor if

fatigue or drowsiness persists or continues to recur

Pregnancy/Breastfeeding

ask a health professional before use.

Keep out of reach of children

In case of overdose, get medical help or contact a doctor or Poison Control Center (1-800-222-1222) right away.

Directions

Adults and children 12 years of age and older: take 1 tablet not more than every 3 to 4 hours

Children under 12 years of age: do not use

Other information

- store at room temperature 68º-77ºF (20º-25ºC)
- avoid excessive heat (greater than 100°F) and humidity
- do not use if carton is opened or if blister unit is broken

Inactive ingredients

croscarmellose sodium, D&C yellow #10 aluminum lake, dicalcium phosphate, FD&C yellow #6 aluminum lake, hypromellose, magnesium stearate, microcrystalline cellulose, polyethylene glycol, silicon dioxide, titanium dioxide

Questions or comments?

Call 1-888-423-0139

Principal Display Panel

Alertness Aid